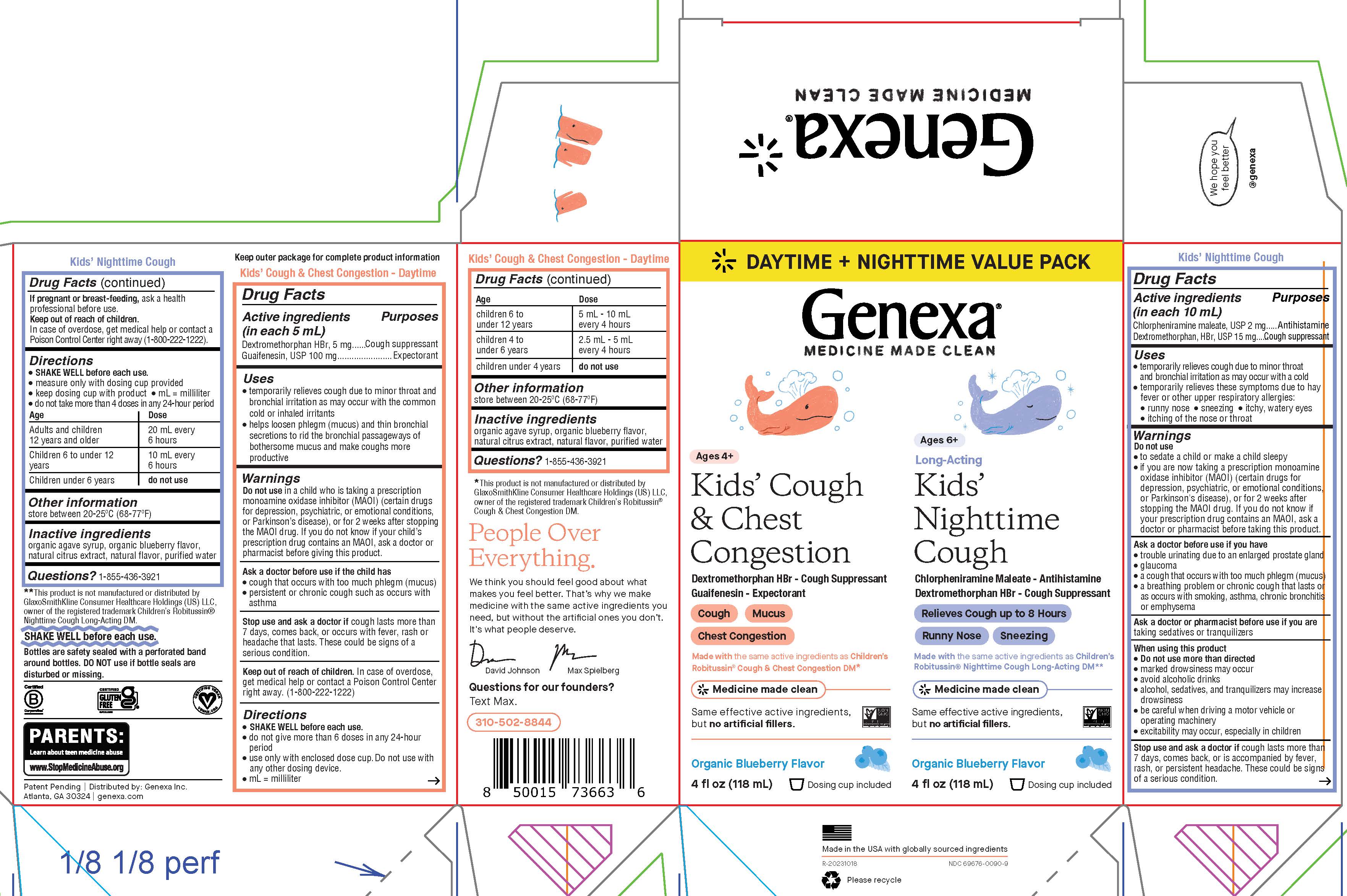 DRUG LABEL: Kids Cough Daytime Nighttime Combo
NDC: 69676-0090 | Form: KIT | Route: ORAL
Manufacturer: Genexa Inc.
Category: otc | Type: HUMAN OTC DRUG LABEL
Date: 20240206

ACTIVE INGREDIENTS: DEXTROMETHORPHAN HYDROBROMIDE 5 mg/5 mL; GUAIFENESIN 100 mg/5 mL; CHLORPHENIRAMINE MALEATE 2 mg/10 mL; DEXTROMETHORPHAN HYDROBROMIDE 15 mg/10 mL
INACTIVE INGREDIENTS: WATER; CITRUS FRUIT; AGAVE TEQUILANA STEM; CITRUS FRUIT; WATER; AGAVE TEQUILANA STEM

Kids' Cough Daytime + Nighttime Combo

Kids' Cough & Chest Congestion

Drug Facts

Active ingredients (in each 5 mL)

Dextromethorphan HBr, 5 mg

Guaifenesin, USP 100 mg

Purposes

Cough suppressant

Expectorant

Uses

• temporarily relieves cough due to minor throat and bronchial irritation as may occur with the common cold or inhaled irritants
• helps loosen phlegm (mucus) and thin bronchial secretions to rid the bronchial passageways of bothersome mucus and make coughs more productive

Warnings

Do not use in a child who is taking a prescription monoamine oxidase inhibitor (MAOI) (certain drugs for depression, psychiatric, or emotional conditions, or Parkinson’s disease), or for 2 weeks after stopping the MAOI drug. If you do not know if your child’s prescription drug contains an MAOI, ask a doctor or pharmacist before giving this product.

Ask a doctor before use if the child has

- cough that occurs with too much phlegm (mucus)
- persistent or chronic cough such as occurs with asthma

Stop use and ask a doctor if cough lasts more than 7 days, comes back, or occurs with fever, rash or headache that lasts. These could be signs of a serious condition.

Keep out of reach of children. In case of overdose, get medical help or contact a Poison Control Center right away. (1-800-222-1222)

Directions

- SHAKE WELL before each use
- do not give more than 6 doses in any 24-hour period
- use only with enclosed dose cup. Do not use with any other dosing device.
- mL = milliliter

Age | Dose
children 6 to under 12 years | 5 mL - 10 mL every 4 hours
children 4 to under 6 years | 2.5 mL - 5 mL every 4 hours
children under 4 years | do not use

Other information

store between 20-25°C (68-77°F)

INACTIVE INGREDIENT

Inactive ingredients organic agave syrup, organic blueberry flavor, natural citrus extract, natural flavor, purified water

Questions?

1-855-436-3921

*This product is not manufactured or distributed by GlaxoSmithKline Consumer Healthcare Holdings (US) LLC, owner of the registered trademark Children's Robitussin® Cough & Chest Congestion DM.

Kids' Nighttime Cough

Drug Facts

Active Ingredients (in each 10 mL)

Chlorpheniramine maleate, USP 2 mg

Dextromethorphan HBr, USP 15 mg

Purposes

Antihistamine

Cough suppressant

Uses

• temporarily relieves cough due to minor throat and bronchial irritation as may occur with a cold
• temporarily relieves these symptoms due to hay fever or other upper respiratory allergies:

• runny nose • sneezing • itchy, watery eyes

• itching of the nose or throat

Warnings

Do not use

• to sedate a child or make a child sleepy
• if you are now taking a prescription monoamine oxidase inhibitor (MAOI) (certain drugs for depression, psychiatric, or emotional conditions, or Parkinson's disease), or for 2 weeks after stopping the MAOI drug. If you do not know if your prescription drug contains an MAOI, ask a doctor or pharmacist before taking this product.

Ask a doctor before use if you have

• trouble urinating due to an enlarged prostate gland
• glaucoma
• a cough that occurs with too much phlegm (mucus)
• a breathing problem or chronic cough that lasts or as occurs with smoking, asthma, chronic bronchitis or emphysema

Ask a doctor or pharmacist before use if you are taking sedatives or tranquilizers

When using this product

• Do not use more than directed
• marked drowsiness may occur
• avoid alcoholic drinks
• alcohol, sedatives, and tranquilizers may increase drowsiness
• be careful when driving a motor vehicle or operating machinery
• excitability may occur, especially in children

Stop use and ask a doctor if cough lasts more than 7 days, comes back, or is accompanied by fever, rash, or persistent headache. These could be signs of a serious condition.

PREGNANCY OR BREAST FEEDING

If pregnant or breast-feeding, ask a health professional before use.

Keep out of reach of children.

In case of overdose, get medical help or contact a Poison Control Center right away (1-800-222-1222).

Directions

- SHAKE WELL before each use.
- measure only with dosing cup provided
- keep dosing cup with product
- mL = milliliter
- do not take more than 4 doses in any 24-hour period

Age | Dose
Adults and children; 12 years and older | 20 mL every; 6 hours
Children 6 to under 12; years | 10 mL every 6 hours
Children under 6 years | do not use

Other information

store between 20-25°C (68-77°F)

Inactive ingredients

organic agave syrup, organic blueberry flavor, natural citrus extract, natural flavor, purified water

Questions? 1-855-436-3921

**This product is not manufactured or distributed by GlaxoSmithKline Consumer Healthcare Holdings (US) LLC, owner of the registered trademark Children's Robitussin® Nighttime Cough Long-Acting DM.

SHAKE WELL before each use.

Bottles are safety sealed with a perforated band around bottles. DO NOT use if bottle seals are disturbed or missing.

Patent Pending | Distributed by: Genexa Inc.

Atlanta, GA 30324 | genexa.com

Made in the USA with globally sourced ingredients

NDC 69676-0090-9

RECENT MAJOR CHANGES

Kids' Cough & Chest Congestion

Directions

SHAKE WELL before each use.
do not give more than 6 doses in any 24-hour period
use only with enclosed dose cup. Do not use with any other dosing device.
mL = milliliter

Age | Dose
children 6 to under 12 years | 5 mL - 10 mL every 4 hours
children 4 to under 6 years | 2.5 mL - 5 mL every 4 hours
children under 4 years | do not use

Kids' Nighttime Cough

Uses

temporarily relieves cough due to minor throat and bronchial irritation as may occur with a cold
temporarily relieves these symptoms due to hay fever or other upper respiratory allergies:

• runny nose • sneezing • itchy, watery eyes

• itching of the nose or throat

Directions

SHAKE WELL before each use.
measure only with dosing cup provided
keep dosing cup with product
mL = milliliter
do not take more than 4 doses in any 24-hour period

Age | Dose
Adults and children; 12 years and older | 20 mL every; 6 hours
Children 6 to under 12; years | 10 mL every 6 hours
Children under 6 years | do not use

PACKAGE LABEL

DAYTIME + NIGHTTIME VALUE PACK

Genexa®

MEDICINE MADE CLEAN

Ages 4+
Kids' Cough & Chest Congestion

Dextromethorphan HBr - Cough Suppressant

Guaifenesin - Expectorant

Cough

Mucus

Chest Congestion

Made with the same active ingredients as Children's Robitussin® Cough & Chest Congestion DM*

Medicine made clean

Same effective active ingredients, but no artificial fillers.

Organic Blueberry Flavor

4 fl oz (118 mL)

Dosing cup included

Ages 6+

Long-Acting
Kids' Nighttime Cough

Chlorpheniramine Maleate - Antihistamine

Dextromethorphan HBr - Cough Suppressant

Relieves Cough up to 8 Hours

Runny Nose

Sneezing

Made with the same active ingredients as Children's Robitussin® Nighttime Cough Long-Acting DM**

Medicine made clean

Same effective active ingredients, but no artificial fillers.

Organic Blueberry Flavor

4 fl oz (118 mL)

Dosing cup included